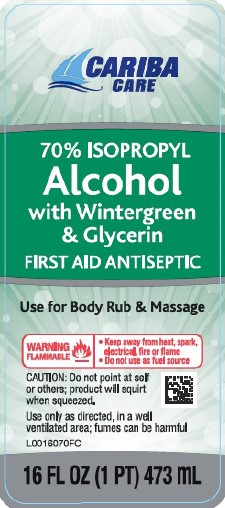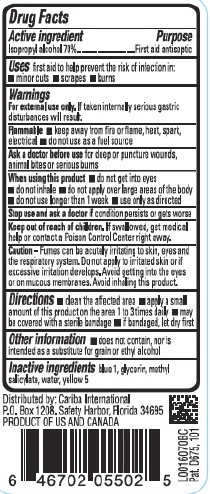 DRUG LABEL: Isopropyl Alcohol
NDC: 67860-845 | Form: LIQUID
Manufacturer: Cariba International
Category: otc | Type: HUMAN OTC DRUG LABEL
Date: 20260129

ACTIVE INGREDIENTS: ISOPROPYL ALCOHOL 70 mL/100 mL
INACTIVE INGREDIENTS: FD&C BLUE NO. 1; GLYCERIN; METHYL SALICYLATE; WATER; FD&C YELLOW NO. 5

Cariba 845.003/845AE
70% IPA, Wintergreen

Active ingredients

Isopropyl alcohol 70%

Purpose

First aid antiseptic

Use

first aid to help prevent the risk of infection in:

- minor cuts
- scrapes
- burns

Warnings

For external use only

Flammable

- Keep away from fire or flame, heat, spark, electrical
- Do not use as a fuel source

Ask a doctor before use

for deep or puncture wounds, animal bites or serious burns

When using this product

- do not get into eyes
- do not inhale
- do not apply over large areas of the body
- do not use longer than 1 week
- use only as directed

Stop use and ask a doctor if

condition persists or gets worse

Keep out of reach of children.

If swallowed, get medical help or contact a Poison Control Center right away.

Caution

Fumes can be acutely irritating to skin, eyes and the respiratory system. Do not apply to irritated skin or if excessive irritation develops. Avoid getting into the eyes or on mucous membranes. Avoid inhaling this product.

Directions

- clean the affected area
- apply a small amount of this product on the area 1 to 3 times daily
- may be covered with a sterile bandage
- if bandaged, let dry first

Other information

- does not contain, nor is intended as a substitute for grain or ethyl alcohol

Inactive ingredients

blue 1, glycerin, methyl salicylate, water, yellow 5

Distributed by: Cariba International

P.O. Box 1208 Safety Harbor Harbor, Florida 34695

PRODUCT OF US AND CANADA

Pat. D675,101

principal display panel

Cariba

Care

70% ISOPROPYL

ALCOHOL

WITH WINTERGREEN AND GLYCERIN

First Aid Antiseptic

Use for Body Rub & Massage

WARNING FLAMMABLE

- Keep away from heat, spark, electrical, fire or flame
- Do not use as fuel source

CAUTION: Do not point at self or others; product will squirt when squeezed.

Use onlyas directed, in a well-ventilated area; fumes may be harmful

16 FL OZ (1 PT) 473 mL